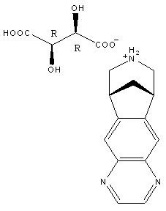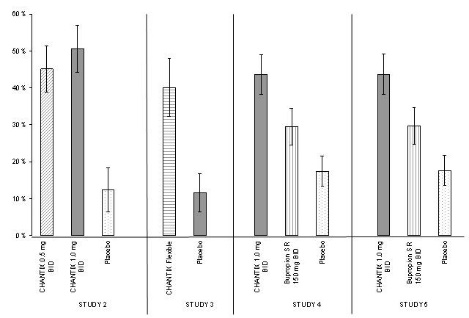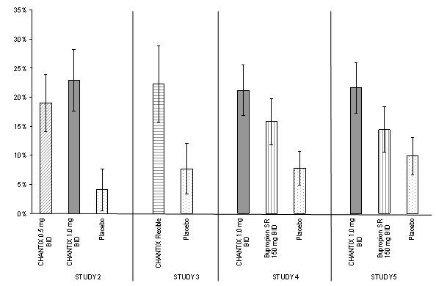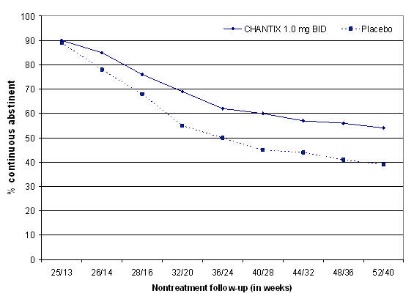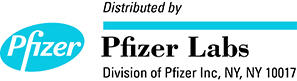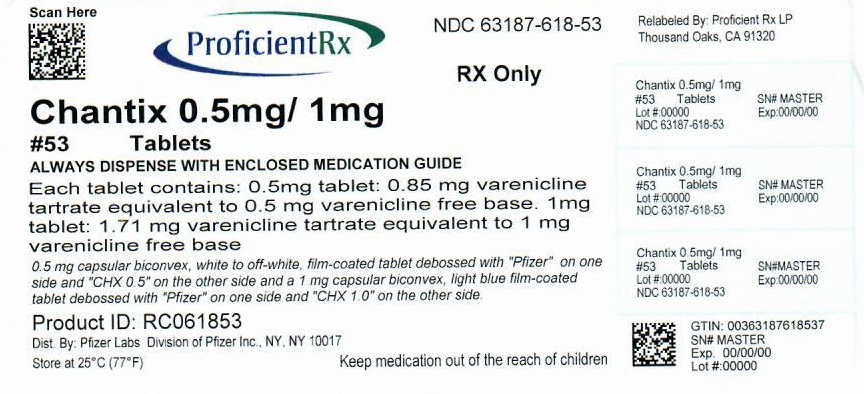 DRUG LABEL: CHANTIX
NDC: 63187-618 | Form: KIT | Route: ORAL
Manufacturer: Proficient Rx LP
Category: prescription | Type: HUMAN PRESCRIPTION DRUG LABEL
Date: 20200201

ACTIVE INGREDIENTS: VARENICLINE TARTRATE 0.5 mg/1 1; VARENICLINE TARTRATE 1 mg/1 1
INACTIVE INGREDIENTS: MICROCRYSTALLINE CELLULOSE; ANHYDROUS DIBASIC CALCIUM PHOSPHATE; CROSCARMELLOSE; SILICON DIOXIDE; MAGNESIUM STEARATE; MICROCRYSTALLINE CELLULOSE; ANHYDROUS DIBASIC CALCIUM PHOSPHATE; CROSCARMELLOSE; SILICON DIOXIDE; MAGNESIUM STEARATE

HIGHLIGHTS OF PRESCRIBING INFORMATION

These highlights do not include all the information needed to use CHANTIX safely and effectively. See full prescribing information for CHANTIX.
CHANTIX® (varenicline) Tablets
Initial U.S. Approval: 2006

WARNING: SERIOUS NEUROPSYCHIATRIC EVENTS

See full prescribing information for complete boxed warning.

- Serious neuropsychiatric events have been reported in patients taking CHANTIX. (5.1 and 6.2)
- Advise patients and caregivers that the patient should stop taking CHANTIX and contact a healthcare provider immediately if agitation, hostility, depressed mood, or changes in behavior or thinking that are not typical for the patient are observed, or if the patient develops suicidal ideation or suicidal behavior while taking CHANTIX or shortly after discontinuing CHANTIX. (5.1 and 6.2)
- Weigh the risks of CHANTIX against benefits of its use. CHANTIX has been demonstrated to increase the likelihood of abstinence from smoking for as long as one year compared to treatment with placebo. The health benefits of quitting smoking are immediate and substantial. (5.1 and 6.2)

RECENT MAJOR CHANGES

Dosage and Administration
Usual Dosage for Adults (2.1) | 10/2014
Warnings and Precautions
Neuropsychiatric Symptoms and Suicidality (5.1) | 09/2014
Seizures (5.2) | 09/2014
Interaction with Alcohol (5.3) | 09/2014

1 INDICATIONS AND USAGE

CHANTIX is a nicotinic receptor partial agonist indicated for use as an aid to smoking cessation treatment. (1 and 2.1)

2 DOSAGE AND ADMINISTRATION

- Begin CHANTIX dosing one week before the date set by the patient to stop smoking. Alternatively, the patient can begin CHANTIX dosing and then quit smoking between days 8 and 35 of treatment. (2.1)
- Starting week: 0.5 mg once daily on days 1–3 and 0.5 mg twice daily on days 4–7. (2.1)
- Continuing weeks: 1 mg twice daily for a total of 12 weeks. (2.1)
- An additional 12 weeks of treatment is recommended for successful quitters to increase likelihood of long-term abstinence. (2.1)
- Renal impairment: Reduce the dose in patients with severe renal impairment (estimated creatinine clearance <30 mL/min). (2.2)
- Consider dose reduction for patients who cannot tolerate adverse effects. (2.1)
- Another attempt at treatment is recommended for those who fail to stop smoking or relapse when factors contributing to the failed attempt have been addressed. (2.1)
- Provide patients with appropriate educational materials and counseling to support the quit attempt. (2.1)

3 DOSAGE FORMS AND STRENGTHS

Tablets: 0.5 mg and 1 mg (3)

4 CONTRAINDICATIONS

History of serious hypersensitivity or skin reactions to CHANTIX. (4)

5 WARNINGS AND PRECAUTIONS

- Seizures: New or worsening seizures have been observed in patients taking CHANTIX. CHANTIX should be used cautiously in patients with a history of seizures or other factors that can lower the seizure threshold. (5.2)
- Interaction with alcohol: Increased effects of alcohol have been reported. Instruct patients to reduce the amount of alcohol they consume until they know whether CHANTIX affects them. (5.3)
- Accidental injury: Accidental injuries (e.g., traffic accidents) have been reported. Instruct patients to use caution driving or operating machinery until they know how CHANTIX may affect them. (5.4)
- Cardiovascular events: A meta-analysis of 15 clinical trials, including a trial in patients with stable cardiovascular disease, demonstrated that while cardiovascular events were infrequent overall, some were reported more frequently in patients treated with CHANTIX. These events occurred primarily in patients with known cardiovascular disease. In both the clinical trial and meta-analysis, all-cause and cardiovascular mortality was lower in patients treated with CHANTIX. Instruct patients to notify their health care providers of new or worsening cardiovascular symptoms and to seek immediate medical attention if they experience signs and symptoms of myocardial infarction or stroke. (5.5 and 6.1)
- Angioedema and hypersensitivity reactions: Such reactions, including angioedema, infrequently life threatening, have been reported. Instruct patients to discontinue CHANTIX and immediately seek medical care if symptoms occur. (5.6 and 6.2)
- Serious skin reactions: Rare, potentially life-threatening skin reactions have been reported. Instruct patients to discontinue CHANTIX and contact a healthcare provider immediately at first appearance of skin rash with mucosal lesions. (5.7 and 6.2)
- Nausea: Nausea is the most common adverse reaction (up to 30% incidence rate). Dose reduction may be helpful. (5.8)

6 ADVERSE REACTIONS

Most common adverse reactions (>5% and twice the rate seen in placebo-treated patients) were nausea, abnormal (e.g., vivid, unusual, or strange) dreams, constipation, flatulence, and vomiting. (6.1)

To report SUSPECTED ADVERSE REACTIONS, contact Pfizer Inc at 1-800-438-1985 or FDA at 1-800-FDA-1088 or www.fda.gov/medwatch.

7 DRUG INTERACTIONS

- Other smoking cessation therapies: Safety and efficacy in combination with other smoking cessation therapies has not been established. Coadministration of varenicline and transdermal nicotine resulted in a high rate of discontinuation due to adverse events. (7.1)
- Effect of smoking cessation: Pharmacokinetics or pharmacodynamics of certain drugs may be altered due to smoking cessation with CHANTIX, necessitating dose adjustment. (7.2)

8 USE IN SPECIFIC POPULATIONS

- Pregnancy: CHANTIX should be used during pregnancy only if the potential benefit justifies the potential risk to the fetus. (8.1)
- Nursing Mothers: Discontinue drug or nursing taking into consideration importance of drug to mother. (8.3)
- Pediatric Use: Safety and effectiveness not established. (8.4)
- Renal Impairment: Dosage adjustment is required for severe renal impairment. (2.2, 8.6)

FULL PRESCRIBING INFORMATION

WARNING: SERIOUS NEUROPSYCHIATRIC EVENTS

Serious neuropsychiatric events including, but not limited to, depression, suicidal ideation, suicide attempt, and completed suicide have been reported in patients taking CHANTIX. Some reported cases may have been complicated by the symptoms of nicotine withdrawal in patients who stopped smoking. Depressed mood may be a symptom of nicotine withdrawal. Depression, rarely including suicidal ideation, has been reported in smokers undergoing a smoking cessation attempt without medication. However, some of these symptoms have occurred in patients taking CHANTIX who continued to smoke.

All patients being treated with CHANTIX should be observed for neuropsychiatric symptoms including changes in behavior, hostility, agitation, depressed mood, and suicide-related events, including ideation, behavior, and attempted suicide. These symptoms, as well as worsening of pre-existing psychiatric illness and completed suicide, have been reported in some patients attempting to quit smoking while taking CHANTIX in the postmarketing experience. When symptoms were reported, most were during CHANTIX treatment, but some were following discontinuation of CHANTIX therapy.

These events have occurred in patients with and without pre-existing psychiatric disease. Patients with serious psychiatric illness such as schizophrenia, bipolar disorder, and major depressive disorder did not participate in the premarketing studies of CHANTIX.

Advise patients and caregivers that the patient should stop taking CHANTIX and contact a healthcare provider immediately if agitation, hostility, depressed mood, or changes in behavior or thinking that are not typical for the patient are observed, or if the patient develops suicidal ideation or suicidal behavior. In many postmarketing cases, resolution of symptoms after discontinuation of CHANTIX was reported, although in some cases the symptoms persisted; therefore, ongoing monitoring and supportive care should be provided until symptoms resolve.

The risks of CHANTIX should be weighed against the benefits of its use. CHANTIX has been demonstrated to increase the likelihood of abstinence from smoking for as long as one year compared to treatment with placebo. The health benefits of quitting smoking are immediate and substantial. [see Warnings and Precautions (5.1) and Adverse Reactions (6.2)]

1 INDICATIONS AND USAGE

CHANTIX is indicated for use as an aid to smoking cessation treatment.

2 DOSAGE AND ADMINISTRATION

2.1 Usual Dosage for Adults

Smoking cessation therapies are more likely to succeed for patients who are motivated to stop smoking and who are provided additional advice and support. Provide patients with appropriate educational materials and counseling to support the quit attempt.

The patient should set a date to stop smoking. Begin CHANTIX dosing one week before this date. Alternatively, the patient can begin CHANTIX dosing and then quit smoking between days 8 and 35 of treatment.

CHANTIX should be taken after eating and with a full glass of water.

The recommended dose of CHANTIX is 1 mg twice daily following a 1-week titration as follows:

Days 1 – 3: | 0.5 mg once daily
Days 4 – 7: | 0.5 mg twice daily
Day 8 – end of treatment: | 1 mg twice daily

Patients should be treated with CHANTIX for 12 weeks. For patients who have successfully stopped smoking at the end of 12 weeks, an additional course of 12 weeks' treatment with CHANTIX is recommended to further increase the likelihood of long-term abstinence.

Patients who are motivated to quit, and who did not succeed in stopping smoking during prior CHANTIX therapy for reasons other than intolerability due to adverse events or who relapsed after treatment, should be encouraged to make another attempt with CHANTIX once factors contributing to the failed attempt have been identified and addressed.

Consider a temporary or permanent dose reduction in patients who cannot tolerate the adverse effects of CHANTIX.

2.2 Dosage in Special Populations

Patients with Impaired Renal Function: No dosage adjustment is necessary for patients with mild to moderate renal impairment. For patients with severe renal impairment (estimated creatinine clearance <30 mL/min), the recommended starting dose of CHANTIX is 0.5 mg once daily. The dose may then be titrated as needed to a maximum dose of 0.5 mg twice a day. For patients with end-stage renal disease undergoing hemodialysis, a maximum dose of 0.5 mg once daily may be administered if tolerated [see Use in Specific Populations (8.6) and Clinical Pharmacology (12.3)].

Elderly and Patients with Impaired Hepatic Function: No dosage adjustment is necessary for patients with hepatic impairment. Because elderly patients are more likely to have decreased renal function, care should be taken in dose selection, and it may be useful to monitor renal function [see Use in Specific Populations (8.5)].

3 DOSAGE FORMS AND STRENGTHS

Capsular, biconvex tablets: 0.5 mg (white to off-white, debossed with "Pfizer" on one side and "CHX 0.5" on the other side) and 1 mg (light blue, debossed with "Pfizer" on one side and "CHX 1.0" on the other side).

4 CONTRAINDICATIONS

CHANTIX is contraindicated in patients with a known history of serious hypersensitivity reactions or skin reactions to CHANTIX.

5 WARNINGS AND PRECAUTIONS

5.1 Neuropsychiatric Symptoms and Suicidality

Serious neuropsychiatric symptoms have been reported in patients being treated with CHANTIX [see Boxed Warning and Adverse Reactions (6.2)]. These postmarketing reports have included changes in mood (including depression and mania), psychosis, hallucinations, paranoia, delusions, homicidal ideation, hostility, agitation, anxiety, and panic, as well as suicidal ideation, suicide attempt, and completed suicide. Some reported cases may have been complicated by the symptoms of nicotine withdrawal in patients who stopped smoking. Depressed mood may be a symptom of nicotine withdrawal. Depression, rarely including suicidal ideation, has been reported in smokers undergoing a smoking cessation attempt without medication. However, some of these symptoms have occurred in patients taking CHANTIX who continued to smoke. When symptoms were reported, most were during CHANTIX treatment, but some were following discontinuation of CHANTIX therapy.

These events have occurred in patients with and without pre-existing psychiatric disease; some patients have experienced worsening of their psychiatric illnesses. All patients being treated with CHANTIX should be observed for neuropsychiatric symptoms or worsening of pre-existing psychiatric illness. Patients with serious psychiatric illness such as schizophrenia, bipolar disorder, and major depressive disorder did not participate in the premarketing studies of CHANTIX. Limited safety data are available from post-marketing smoking cessation studies in two patient groups: 1) patients with major depressive disorder, and 2) patients with stable schizophrenia or schizoaffective disorder [see Adverse Reactions (6.1), Clinical Studies (14.5)].

Some reported neuropsychiatric events, including unusual and sometimes aggressive behavior directed to oneself or others, may have been worsened by concomitant use of alcohol [see Interaction with Alcohol (5.3), Adverse Reactions (6.2)].

Advise patients and caregivers that the patient should stop taking CHANTIX and contact a healthcare provider immediately if agitation, depressed mood, changes in behavior or thinking that are not typical for the patient are observed, or if the patient develops suicidal ideation or suicidal behavior. In many postmarketing cases, resolution of symptoms after discontinuation of CHANTIX was reported, although in some cases the symptoms persisted, therefore, ongoing monitoring and supportive care should be provided until symptoms resolve.

The risks of CHANTIX should be weighed against the benefits of its use. CHANTIX has been demonstrated to increase the likelihood of abstinence from smoking for as long as one year compared to treatment with placebo. The health benefits of quitting smoking are immediate and substantial.

Since the initial signal of neuropsychiatric symptoms and suicidality emerged, additional analyses and studies have been conducted to further evaluate this association.

Analyses of clinical trials
A meta-analysis of 5 randomized, double blind, placebo controlled trials, including 1907 patients (1130 CHANTIX, 777 placebo) was conducted to assess suicidal ideation and behavior as reported on the Columbia-Suicide Severity Rating Scale (C SSRS). This meta-analysis included one trial (N=127) in patients with a history of schizophrenia or schizoaffective disorder and another trial (N=525) in patients with a history of depression. The results showed no increase in the incidence of suicidal ideation and/or behavior in patients treated with CHANTIX compared to patients treated with placebo, with a Risk Ratio (RR) of 0.79 (95% Confidence Interval [CI]: 0.46, 1.36), as shown in Table 1. Forty-eight (48) of the 55 patients who reported suicidal ideation or behavior (24 CHANTIX, 24 placebo) were observed in the two trials that enrolled patients with a history of schizophrenia, schizoaffective disorder, or depression. Few events were observed in the other three trials (4 CHANTIX, 3 placebo).

Table 1. Number of Patients and Risk Ratio for Suicidal Ideation and/or Behavior Reported on C-SSRS from a Meta-Analysis of 5 Clinical Trials Comparing CHANTIX to Placebo
 | CHANTIX (N=1130) | Placebo (N=777)
Patients with Suicidal ideation and/or behavior [Of the events, one patient in each treatment arm reported suicidal behavior] [n (%)] [Patients with events up to 30 days after treatment; % are not weighted by study] | 28 (2.5) | 27 (3.5)
Patient-years of exposure | 325 | 217
Risk Ratio [# RR of incidence rates per 100 patient years] (RR; 95% CI) | 0.79 (0.46, 1.36)

A pooled analysis of 18 double-blind, randomized, placebo-controlled clinical trials, which includes the 5 trials that collected C-SSRS described in Table 1, was conducted to assess the psychiatric safety of CHANTIX. This pooled analysis included 8521 patients (5072 CHANTIX, 3449 placebo), some of whom had psychiatric conditions at baseline. Table 2 describes the most frequently (≥ 1%) reported adverse events related to psychiatric safety. The results showed a similar incidence of common psychiatric events in patients treated with CHANTIX compared to patients treated with placebo.

Table 2. Psychiatric Adverse Events Occurring in ≥ 1% of Patients from Pooled Analysis of 18 Clinical Trials
 | CHANTIX (N=5072) | Placebo (N=3449)
Anxiety disorders and symptoms | 253 (5.0) | 206 (6.0)
Depressed mood disorders and disturbances | 179 (3.5) | 108 (3.1)
Mood disorders and disturbances NEC [NEC = Not Elsewhere Classified Counts (percentages) corresponds to the number of patients reporting the event] | 116 (2.3) | 53 (1.5)

Observational Studies

Four observational studies, each including 10,000 to 30,000 users of CHANTIX in the adjusted analyses, compared the risk of selected serious neuropsychiatric events (neuropsychiatric hospitalizations, fatal and non-fatal self-harm), between CHANTIX users and prescription NRT or bupropion users. All studies were retrospective cohort studies and included patients with and without a psychiatric history.

Two of the studies found no difference in risk of neuropsychiatric hospitalizations between CHANTIX users and nicotine patch users (Hazard Ratio [HR] 1.14; 95% Confidence Interval [CI]: 0.56–2.34 in the first study, and 0.76; 95% CI: 0.40–1.46 in the second study). However, neither study validated the diagnostic codes used to identify outcomes against medical records. A third study reported no difference in risk of psychiatric adverse events diagnosed during an emergency department visit or inpatient admission between CHANTIX users and bupropion users (HR 0.85; 95% CI: 0.55–1.30). Bupropion has also been associated with neuropsychiatric adverse events. A fourth study examined risk of fatal and non-fatal self-harm in users of CHANTIX compared to users of NRT. Although the occurrence of detected suicide was rare during the three months after patients initiated any drug treatment (two cases in 31,260 CHANTIX users and six cases in 81,545 NRT users), this study has important limitations. Most importantly, these data were captured following public awareness of reports of neuropsychiatric adverse events in CHANTIX users. CHANTIX users had fewer comorbid conditions that could put them at risk for neuropsychiatric adverse events, suggesting that patients with a history of neuropsychiatric illness were preferentially prescribed NRT, and healthier patients were preferentially prescribed CHANTIX.

Outcomes examined in these studies did not include the full range of neuropsychiatric adverse events that have been reported.

5.2 Seizures

During clinical trials and the post-marketing experience, there have been reports of seizures in patients treated with CHANTIX. Some patients had no history of seizures, whereas others had a history of seizure disorder that was remote or well-controlled. In most cases, the seizure occurred within the first month of therapy. Weigh this potential risk against the potential benefits before prescribing CHANTIX in patients with a history of seizures or other factors that can lower the seizure threshold. Advise patients to discontinue CHANTIX and contact a healthcare provider immediately if they experience a seizure while on treatment [see Adverse Reactions (6.2)].

5.3 Interaction with Alcohol

There have been post-marketing reports of patients experiencing increased intoxicating effects of alcohol while taking CHANTIX. Some cases described unusual and sometimes aggressive behavior, and were often accompanied by amnesia for the events. Advise patients to reduce the amount of alcohol they consume while taking CHANTIX until they know whether CHANTIX affects their tolerance for alcohol [see Adverse Reactions (6.2)].

5.4 Accidental Injury

There have been postmarketing reports of traffic accidents, near-miss incidents in traffic, or other accidental injuries in patients taking CHANTIX. In some cases, the patients reported somnolence, dizziness, loss of consciousness or difficulty concentrating that resulted in impairment, or concern about potential impairment, in driving or operating machinery. Advise patients to use caution driving or operating machinery or engaging in other potentially hazardous activities until they know how CHANTIX may affect them.

5.5 Cardiovascular Events

In a placebo-controlled clinical trial of CHANTIX administered to patients with stable cardiovascular disease, with approximately 350 patients per treatment arm, all-cause and cardiovascular mortality was lower in patients treated with CHANTIX, but certain nonfatal cardiovascular events occurred more frequently in patients treated with CHANTIX than in patients treated with placebo [see Clinical Trials Experience (6.1)]. Table 3 below shows the incidence of deaths and of selected nonfatal serious cardiovascular events occurring more frequently in the CHANTIX arm compared to the placebo arm. These events were adjudicated by an independent blinded committee. Nonfatal serious cardiovascular events not listed occurred at the same incidence or more commonly in the placebo arm. Patients with more than one cardiovascular event of the same type are counted only once per row. Some of the patients requiring coronary revascularization underwent the procedure as part of management of nonfatal MI and hospitalization for angina.

Table 3. Mortality and Adjudicated Nonfatal Serious Cardiovascular Events in the Placebo-Controlled CHANTIX Trial in Patients with Stable Cardiovascular Disease
Mortality and Cardiovascular Events | CHANTIX (N=353) n (%) | Placebo (N=350) n (%)
Mortality (Cardiovascular & All-cause up to 52 wks)
Cardiovascular death | 1 (0.3) | 2 (0.6)
All-cause mortality | 2 (0.6) | 5 (1.4)
Nonfatal Cardiovascular Events (rate on CHANTIX > Placebo)
Up to 30 days after treatment
Nonfatal myocardial infarction | 4 (1.1) | 1 (0.3)
Nonfatal Stroke | 2 (0.6) | 0 (0)
Beyond 30 days after treatment & up to 52 weeks
Nonfatal myocardial infarction | 3 (0.8) | 2 (0.6)
Need for coronary revascularization | 7 (2.0) | 2 (0.6)
Hospitalization for angina pectoris | 6 (1.7) | 4 (1.1)
Transient ischemia attack | 1 (0.3) | 0 (0)
New diagnosis of peripheral vascular disease (PVD) or admission for a PVD procedure | 5 (1.4) | 2 (0.6)

A meta-analysis of 15 clinical trials of ≥ 12 weeks treatment duration, including 7002 patients (4190 CHANTIX, 2812 placebo), was conducted to systematically assess the cardiovascular safety of CHANTIX. The study in patients with stable cardiovascular disease described above was included in the meta-analysis. There were lower rates of all-cause mortality (CHANTIX 6 [0.14%]; placebo 7 [0.25%]) and cardiovascular mortality (CHANTIX 2 [0.05%]; placebo 2 [0.07%]) in the CHANTIX arms compared with the placebo arms in the meta-analysis.

The key cardiovascular safety analysis included occurrence and timing of a composite endpoint of Major Adverse Cardiovascular Events (MACE), defined as cardiovascular death, nonfatal MI, and nonfatal stroke. These events included in the endpoint were adjudicated by a blinded, independent committee. Overall, a small number of MACE occurred in the trials included in the meta-analysis, as described in Table 4. These events occurred primarily in patients with known cardiovascular disease.

Table 4. Number of MACE cases, Hazard Ratio and Rate Difference in a Meta-Analysis of 15 Clinical Trials Comparing CHANTIX to Placebo [Includes MACE occurring up to 30 days post treatment.]
 | CHANTIX N=4190 | Placebo N=2812
MACE cases, n (%) | 13 (0.31%) | 6 (0.21%)
Patient-years of exposure | 1316 | 839
Hazard Ratio (95% CI)
 | 1.95 (0.79, 4.82)
Rate Difference per 1,000 patient-years (95% CI)
 | 6.30 (-2.40, 15.10)

The meta-analysis showed that exposure to CHANTIX resulted in a hazard ratio for MACE of 1.95 (95% confidence interval from 0.79 to 4.82) for patients up to 30 days after treatment; this is equivalent to an estimated increase of 6.3 MACE events per 1,000 patient-years of exposure. The meta-analysis showed higher rates of CV endpoints in patients on CHANTIX relative to placebo across different time frames and pre-specified sensitivity analyses, including various study groupings and CV outcomes. Although these findings were not statistically significant they were consistent. Because the number of events was small overall, the power for finding a statistically significant difference in a signal of this magnitude is low.

CHANTIX was not studied in patients with unstable cardiovascular disease or cardiovascular events occurring within two months before screening. Patients should be advised to notify a health care provider of new or worsening symptoms of cardiovascular disease. The risks of CHANTIX should be weighed against the benefits of its use in smokers with cardiovascular disease. Smoking is an independent and major risk factor for cardiovascular disease. CHANTIX has been demonstrated to increase the likelihood of abstinence from smoking for as long as one year compared to treatment with placebo.

5.6 Angioedema and Hypersensitivity Reactions

There have been postmarketing reports of hypersensitivity reactions including angioedema in patients treated with CHANTIX [see Adverse Reactions (6.2), and Patient Counseling Information (17)]. Clinical signs included swelling of the face, mouth (tongue, lips, and gums), extremities, and neck (throat and larynx). There were infrequent reports of life-threatening angioedema requiring emergent medical attention due to respiratory compromise. Instruct patients to discontinue CHANTIX and immediately seek medical care if they experience these symptoms.

5.7 Serious Skin Reactions

There have been postmarketing reports of rare but serious skin reactions, including Stevens-Johnson Syndrome and erythema multiforme, in patients using CHANTIX [see Adverse Reactions (6.2)]. As these skin reactions can be life-threatening, instruct patients to stop taking CHANTIX and contact a healthcare provider immediately at the first appearance of a skin rash with mucosal lesions or any other signs of hypersensitivity.

5.8 Nausea

Nausea was the most common adverse reaction reported with CHANTIX treatment. Nausea was generally described as mild or moderate and often transient; however, for some patients, it was persistent over several months. The incidence of nausea was dose-dependent. Initial dose-titration was beneficial in reducing the occurrence of nausea. For patients treated to the maximum recommended dose of 1 mg twice daily following initial dosage titration, the incidence of nausea was 30% compared with 10% in patients taking a comparable placebo regimen. In patients taking CHANTIX 0.5 mg twice daily following initial titration, the incidence was 16% compared with 11% for placebo. Approximately 3% of patients treated with CHANTIX 1 mg twice daily in studies involving 12 weeks of treatment discontinued treatment prematurely because of nausea. For patients with intolerable nausea, a dose reduction should be considered.

6 ADVERSE REACTIONS

The following serious adverse reactions were reported in postmarketing experience and are discussed in greater detail in other sections of the labeling:

- Neuropsychiatric symptoms and suicidality [see Boxed Warning and Warnings and Precautions (5.1)]
- Seizures [see Warnings and Precautions (5.2)]
- Interaction with Alcohol [see Warnings and Precautions (5.3)]
- Accidental injury [see Warnings and Precautions (5.4)]
- Cardiovascular Events [see Warnings and Precautions (5.5)]
- Angioedema and hypersensitivity reactions [see Warnings and Precautions (5.6)]
- Serious skin reactions [see Warnings and Precautions (5.7)]

In the placebo-controlled premarketing studies, the most common adverse events associated with CHANTIX (>5% and twice the rate seen in placebo-treated patients) were nausea, abnormal (vivid, unusual, or strange) dreams, constipation, flatulence, and vomiting.

The treatment discontinuation rate due to adverse events in patients dosed with 1 mg twice daily was 12% for CHANTIX, compared to 10% for placebo in studies of three months' treatment. In this group, the discontinuation rates that are higher than placebo for the most common adverse events in CHANTIX-treated patients were as follows: nausea (3% vs. 0.5% for placebo), insomnia (1.2% vs. 1.1% for placebo), and abnormal dreams (0.3% vs. 0.2% for placebo).

Smoking cessation, with or without treatment, is associated with nicotine withdrawal symptoms and has also been associated with the exacerbation of underlying psychiatric illness.

6.1 Clinical Trials Experience

Because clinical trials are conducted under widely varying conditions, the adverse reactions rates observed in the clinical studies of a drug cannot be directly compared to rates in the clinical trials of another drug and may not reflect the rates observed in clinical practice.

During the premarketing development of CHANTIX, over 4500 subjects were exposed to CHANTIX, with over 450 treated for at least 24 weeks and approximately 100 for a year. Most study participants were treated for 12 weeks or less.

The most common adverse event associated with CHANTIX treatment is nausea, occurring in 30% of patients treated at the recommended dose, compared with 10% in patients taking a comparable placebo regimen [see Warnings and Precautions (5.6)].

Table 5 shows the adverse events for CHANTIX and placebo in the 12- week fixed dose premarketing studies with titration in the first week [Studies 2 (titrated arm only), 4, and 5]. Adverse events were categorized using the Medical Dictionary for Regulatory Activities (MedDRA, Version 7.1).

MedDRA High Level Group Terms (HLGT) reported in ≥ 5% of patients in the CHANTIX 1 mg twice daily dose group, and more commonly than in the placebo group, are listed, along with subordinate Preferred Terms (PT) reported in ≥ 1% of CHANTIX patients (and at least 0.5% more frequent than placebo). Closely related Preferred Terms such as 'Insomnia', 'Initial insomnia', 'Middle insomnia', 'Early morning awakening' were grouped, but individual patients reporting two or more grouped events are only counted once.

Table 5: Common Treatment Emergent AEs (%) in the Fixed-Dose, Placebo-Controlled Studies (HLGTs ≥ 5% of patients in the 1 mg BID CHANTIX Group and more commonly than placebo and PT ≥ 1% in the 1 mg BID CHANTIX Group, and 1 mg BID CHANTIX at least 0.5% more than Placebo)
SYSTEM ORGAN CLASS High Level Group Term | CHANTIX 0.5 mg BID | CHANTIX 1 mg BID | Placebo
Preferred Term | N=129 | N=821 | N=805
GASTROINTESTINAL (GI)
GI Signs and Symptoms
Nausea | 16 | 30 | 10
Abdominal Pain [Includes PTs Abdominal (pain, pain upper, pain lower, discomfort, tenderness, distension) and Stomach discomfort] | 5 | 7 | 5
Flatulence | 9 | 6 | 3
Dyspepsia | 5 | 5 | 3
Vomiting | 1 | 5 | 2
GI Motility/Defecation Conditions
Constipation | 5 | 8 | 3
Gastroesophageal reflux disease | 1 | 1 | 0
Salivary Gland Conditions
Dry mouth | 4 | 6 | 4
PSYCHIATRIC DISORDERS
Sleep Disorder/Disturbances
Insomnia [Includes PTs Insomnia/Initial insomnia/Middle insomnia/Early morning awakening] | 19 | 18 | 13
Abnormal dreams | 9 | 13 | 5
Sleep disorder | 2 | 5 | 3
Nightmare | 2 | 1 | 0
NERVOUS SYSTEM
Headaches
Headache | 19 | 15 | 13
Neurological Disorders NEC
Dysgeusia | 8 | 5 | 4
Somnolence | 3 | 3 | 2
Lethargy | 2 | 1 | 0
GENERAL DISORDERS
General Disorders NEC
Fatigue/Malaise/Asthenia | 4 | 7 | 6
RESPIR/THORACIC/MEDIAST
Respiratory Disorders NEC
Rhinorrhea | 0 | 1 | 0
Dyspnea | 2 | 1 | 1
Upper Respiratory Tract Disorder | 7 | 5 | 4
SKIN/SUBCUTANEOUS TISSUE
Epidermal and Dermal Conditions
Rash | 1 | 3 | 2
Pruritis | 0 | 1 | 1
METABOLISM & NUTRITION
Appetite/General Nutrit. Disorders
Increased appetite | 4 | 3 | 2
Decreased appetite/Anorexia | 1 | 2 | 1

The overall pattern and frequency of adverse events during the longer-term premarketing trials was similar to those described in Table 5, though several of the most common events were reported by a greater proportion of patients with long-term use (e.g., nausea was reported in 40% of patients treated with CHANTIX 1 mg twice daily in a one-year study, compared to 8% of placebo-treated patients).

Following is a list of treatment-emergent adverse events reported by patients treated with CHANTIX during all premarketing clinical trials and updated based on pooled data from 18 placebo-controlled pre- and post-marketing studies, including approximately 5,000 patients treated with varenicline. Adverse events were categorized using MedDRA, Version 16.0. The listing does not include those events already listed in the previous tables or elsewhere in labeling, those events for which a drug cause was remote, those events which were so general as to be uninformative, and those events reported only once which did not have a substantial probability of being acutely life-threatening.

Blood and Lymphatic System Disorders. Infrequent: anemia, lymphadenopathy. Rare: leukocytosis, splenomegaly, thrombocytopenia.

Cardiac Disorders. Infrequent: angina pectoris, myocardial infarction, palpitations, tachycardia. Rare: acute coronary syndrome, arrhythmia, atrial fibrillation, bradycardia, cardiac flutter, cor pulmonale, coronary artery disease, ventricular extrasystoles.

Ear and Labyrinth Disorders. Infrequent: tinnitus, vertigo. Rare: deafness, Meniere's disease.

Endocrine Disorders. Infrequent: thyroid gland disorders.

Eye Disorders. Infrequent: conjunctivitis, eye irritation, eye pain, vision blurred, visual impairment. Rare: blindness transient, cataract subcapsular, dry eye, night blindness, ocular vascular disorder, photophobia, vitreous floaters.

Gastrointestinal Disorders. Frequent: diarrhea, toothache. Infrequent: dysphagia, eructation, gastritis, gastrointestinal hemorrhage, mouth ulceration. Rare: enterocolitis, esophagitis, gastric ulcer, intestinal obstruction, pancreatitis acute.

General Disorders and Administration Site Conditions. Frequent: chest pain. Infrequent: chest discomfort, chills, edema, influenza-like illness, pyrexia.

Hepatobiliary Disorders. Rare: gall bladder disorder.

Investigations. Frequent: liver function test abnormal, weight increased. Infrequent: electrocardiogram abnormal. Rare: muscle enzyme increased, urine analysis abnormal.

Metabolism and Nutrition Disorders. Infrequent: diabetes mellitus, hypoglycemia. Rare: hyperlipidemia, hypokalemia.

Musculoskeletal and Connective Tissue Disorders. Frequent: arthralgia, back pain, myalgia. Infrequent: arthritis, muscle cramp, musculoskeletal pain. Rare: myositis, osteoporosis.

Nervous System Disorders. Frequent: disturbance in attention, dizziness. Infrequent: amnesia, convulsion, migraine, parosmia, syncope, tremor. Rare: balance disorder, cerebrovascular accident, dysarthria, mental impairment, multiple sclerosis, VIIth nerve paralysis, nystagmus, psychomotor hyperactivity, psychomotor skills impaired, restless legs syndrome, sensory disturbance, transient ischemic attack, visual field defect.

Psychiatric Disorders. Infrequent: dissociation, libido decreased, mood swings, thinking abnormal. Rare: bradyphrenia, disorientation, euphoric mood.

Renal and Urinary Disorders. Infrequent: nocturia, pollakiuria, urine abnormality. Rare: nephrolithiasis, polyuria, renal failure acute, urethral syndrome, urinary retention.

Reproductive System and Breast Disorders. Frequent: menstrual disorder. Infrequent: erectile dysfunction. Rare: sexual dysfunction.

Respiratory, Thoracic and Mediastinal Disorders. Frequent: respiratory disorders. Infrequent: asthma, epistaxis, rhinitis allergic, upper respiratory tract inflammation. Rare: pleurisy, pulmonary embolism.

Skin and Subcutaneous Tissue Disorders. Infrequent: acne, dry skin, eczema, erythema, hyperhidrosis, urticaria. Rare: photosensitivity reaction, psoriasis.

Vascular Disorders. Infrequent: hot flush. Rare: thrombosis.

CHANTIX has also been studied in postmarketing trials including (1) a trial conducted in patients with chronic obstructive pulmonary disease (COPD), (2) a trial conducted in generally healthy patients (similar to those in the premarketing studies) in which they were allowed to select a quit date between days 8 and 35 of treatment ("alternative quit date instruction trial"), (3) a trial conducted in patients who did not succeed in stopping smoking during prior CHANTIX therapy, or who relapsed after treatment ("re-treatment trial"), (4) a trial conducted in patients with stable cardiovascular disease, (5) a trial conducted in patients with stable schizophrenia or schizoaffective disorder and (6) a trial conducted in patients with major depressive disorder.

Adverse events in the trial of patients with COPD, in the alternative quit date instruction trial, were quantitatively and qualitatively similar to those observed in premarketing studies. In the re-treatment trial, the profile of common adverse events was similar to that previously reported, but, in addition, varenicline-treated patients also commonly reported diarrhea (6% vs 4% in placebo-treated patients), depressed mood disorders and disturbances (6% vs 1%), and other mood disorders and disturbances (5% vs 2%).

In the trial of patients with stable cardiovascular disease, more types and a greater number of cardiovascular events were reported compared to premarketing studies. Treatment-emergent (on-treatment or 30 days after treatment) cardiovascular events reported with a frequency ≥ 1% in either treatment group in this study were angina pectoris (3.7% and 2.0% for varenicline and placebo, respectively), chest pain (2.5% vs. 2.3%), peripheral edema (2.0% vs. 1.1%), hypertension (1.4% vs. 2.6%), and palpitations (0.6 % vs. 1.1%). Deaths and serious cardiovascular events occurring over the 52 weeks of the study (treatment emergent and non-treatment emergent) were adjudicated by a blinded, independent committee. The following treatment-emergent adjudicated events occurred with a frequency ≥1% in either treatment group: nonfatal MI (1.1% vs. 0.3% for varenicline and placebo, respectively), and hospitalization for angina pectoris (0.6% vs. 1.1%). During non-treatment follow up to 52 weeks, the adjudicated events included need for coronary revascularization (2.0% vs. 0.6%), hospitalization for angina pectoris (1.7% vs. 1.1%), and new diagnosis of peripheral vascular disease (PVD) or admission for a PVD procedure (1.4% vs. 0.6%). Some of the patients requiring coronary revascularization underwent the procedure as part of management of nonfatal MI and hospitalization for angina. Cardiovascular death occurred in 0.3% of patients in the varenicline arm and 0.6% of patients in the placebo arm over the course of the 52-week study.

In the trial of patients with stable schizophrenia or schizoaffective disorder, 128 smokers on antipsychotic medication were randomized 2:1 to varenicline (1 mg twice daily) or placebo for 12 weeks with 12-week non-drug follow-up. The most common adverse events in patients taking varenicline were nausea (24% vs. 14.0% on placebo), headache (11% vs. 19% on placebo) and vomiting (11% vs. 9% on placebo). Among reported neuropsychiatric adverse events, insomnia was the only event that occurred in either treatment group in ≥5% of subjects at a rate higher in the varenicline group than in placebo (10% vs. 5%). These common and neuropsychiatric adverse events occurred on treatment or within 30 days after the last dose of study drug. There was no consistent worsening of schizophrenia in either treatment group as measured by the Positive and Negative Syndrome Scale. There were no overall changes in extra-pyramidal signs, as measured by the Simpson-Angus Rating Scale. The Columbia-Suicide Severity Rating Scale was administered at baseline and at clinic visits during the treatment and non-treatment follow-up phases. Over half of the patients had a lifetime history of suicidal behavior and/or ideation (62% on varenicline vs. 51% on placebo), but at baseline, no patients in the varenicline group reported suicidal behavior and/or ideation vs. one patient in the placebo group (2%). Suicidal behavior and/or ideation were reported in 11% of the varenicline-treated and 9% of the placebo-treated patients during the treatment phase. During the post-treatment phase, suicidal behavior and/or ideation were reported in 11% of patients in the varenicline group and 5% of patients in the placebo group. Many of the patients reporting suicidal behavior and ideation in the follow-up phase had not reported such experiences in the treatment phase. However, no new suicidal ideation or behavior emerged in either treatment group shortly (within one week) after treatment discontinuation (a phenomenon noted in post-marketing reporting). There were no completed suicides. There was one suicide attempt in a varenicline-treated patient. The limited data available from this single smoking cessation study are not sufficient to allow conclusions to be drawn.

In the trial of patients with major depressive disorder, the most common adverse events (≥ 10%) in subjects taking varenicline were nausea (27% vs. 10% on placebo), headache (17 vs 11%), abnormal dreams (11% vs 8%), insomnia (11% vs 5%) and irritability (11% vs. 8%). Additionally, the following psychiatric AEs were reported in ≥ 2% of patients in either treatment group (varenicline or placebo, respectively): anxiety (7% vs. 9%), agitation (7% vs. 4%), depressed mood disorders and disturbances (11% vs. 9%), tension (4% vs. 3%), hostility (2% vs. 0.4%) and restlessness (2% vs. 2%). Patients treated with varenicline were more likely than patients treated with placebo to report one of various events related to hostility and aggression (3% vs 1%). Psychiatric scales showed no differences between the varenicline and placebo groups and no overall worsening of depression during the study in either treatment group. The percentage of subjects with suicidal ideation and/or behavior was similar between the varenicline and placebo groups during treatment (6% and 8%, respectively) and the non-treatment follow-up (6% and 6%, respectively). There was one event of intentional self-injury/possible suicide attempt during treatment (Day 73) in a subject in the placebo group. Suicide could not be ruled out in one subject who died by an overdose of illicit drugs 76 days after last dose of study drug in the varenicline group.

6.2 Postmarketing Experience

The following adverse events have been reported during post-approval use of CHANTIX. Because these events are reported voluntarily from a population of uncertain size, it is not possible to reliably estimate their frequency or establish a causal relationship to drug exposure.

There have been reports of depression, mania, psychosis, hallucinations, paranoia, delusions, homicidal ideation, aggression, hostility, anxiety, and panic, as well as suicidal ideation, suicide attempt, and completed suicide in patients attempting to quit smoking while taking CHANTIX [see Boxed Warning, Warnings and Precautions (5.1)]. Smoking cessation with or without treatment is associated with nicotine withdrawal symptoms and the exacerbation of underlying psychiatric illness. Not all patients had known pre-existing psychiatric illness and not all had discontinued smoking.

There have been post-marketing reports of new or worsening seizures in patients treated with CHANTIX [see Warnings and Precautions (5.2)].

There have been post-marketing reports of patients experiencing increased intoxicating effects of alcohol while taking CHANTIX. Some reported neuropsychiatric events, including unusual and sometimes aggressive behavior [see Warnings and Precautions (5.1) and (5.3)].

There have been reports of hypersensitivity reactions, including angioedema [see Warnings and Precautions (5.6)].

There have also been reports of serious skin reactions, including Stevens- Johnson Syndrome and erythema multiforme, in patients taking CHANTIX [see Warnings and Precautions (5.7)].

There have been reports of myocardial infarction (MI) and cerebrovascular accident (CVA) including ischemic and hemorrhagic events in patients taking CHANTIX. In the majority of the reported cases, patients had pre-existing cardiovascular disease and/or other risk factors. Although smoking is a risk factor for MI and CVA, based on temporal relationship between medication use and events, a contributory role of varenicline cannot be ruled out.

7 DRUG INTERACTIONS

Based on varenicline characteristics and clinical experience to date, CHANTIX has no clinically meaningful pharmacokinetic drug interactions [see Clinical Pharmacology (12.3)].

7.1 Use With Other Drugs for Smoking Cessation

Safety and efficacy of CHANTIX in combination with other smoking cessation therapies have not been studied.

Bupropion: Varenicline (1 mg twice daily) did not alter the steady-state pharmacokinetics of bupropion (150 mg twice daily) in 46 smokers. The safety of the combination of bupropion and varenicline has not been established.

Nicotine replacement therapy (NRT): Although co-administration of varenicline (1 mg twice daily) and transdermal nicotine (21 mg/day) for up to 12 days did not affect nicotine pharmacokinetics, the incidence of nausea, headache, vomiting, dizziness, dyspepsia, and fatigue was greater for the combination than for NRT alone. In this study, eight of twenty-two (36%) patients treated with the combination of varenicline and NRT prematurely discontinued treatment due to adverse events, compared to 1 of 17 (6%) of patients treated with NRT and placebo.

7.2 Effect of Smoking Cessation on Other Drugs

Physiological changes resulting from smoking cessation, with or without treatment with CHANTIX, may alter the pharmacokinetics or pharmacodynamics of certain drugs (e.g., theophylline, warfarin, insulin) for which dosage adjustment may be necessary.

8 USE IN SPECIFIC POPULATIONS

8.1 Pregnancy

TERATOGENIC EFFECTS

Pregnancy Category C.

There are no adequate and well-controlled studies of CHANTIX use in pregnant women. In animal studies, CHANTIX caused decreased fetal weights, increased auditory startle response, and decreased fertility in offspring. CHANTIX should be used during pregnancy only if the potential benefit justifies the potential risk to the fetus.

In reproductive and developmental toxicity studies, pregnant rats and rabbits received varenicline succinate during organogenesis at oral doses up to 15 and 30 mg/kg/day, respectively. These exposures were 36 (rats) and 50 (rabbits) times the human exposure (based on AUC) at the maximum recommended human dose (MRHD) of 1 mg twice daily. While no fetal structural abnormalities occurred in either species, reduced fetal weights occurred in rabbits at the highest dose (exposures 50 times the human exposure at the MRHD based on AUC). Fetal weight reduction did not occur at animal exposures 23 times the human exposure at the MRHD based on AUC.

In a pre- and postnatal development study, pregnant rats received up to 15 mg/kg/day of oral varenicline succinate from organogenesis through lactation. These resulted in exposures up to 36 times the human exposure (based on AUC) at the MRHD of 1 mg twice daily. Decreased fertility and increased auditory startle response occurred in offspring.

8.3 Nursing Mothers

It is not known whether CHANTIX is excreted in human milk. In animal studies varenicline was excreted in milk of lactating animals. Because many drugs are excreted in human milk and because of the potential for serious adverse reactions in nursing infants from CHANTIX, a decision should be made whether to discontinue nursing or to discontinue the drug, taking into account the importance of the drug to the mother.

8.4 Pediatric Use

Safety and effectiveness of CHANTIX in pediatric patients have not been established.

8.5 Geriatric Use

A combined single- and multiple-dose pharmacokinetic study demonstrated that the pharmacokinetics of 1 mg varenicline given once daily or twice daily to 16 healthy elderly male and female smokers (aged 65–75 yrs) for 7 consecutive days was similar to that of younger subjects. No overall differences in safety or effectiveness were observed between these subjects and younger subjects, and other reported clinical experience has not identified differences in responses between the elderly and younger patients, but greater sensitivity of some older individuals cannot be ruled out.

Varenicline is known to be substantially excreted by the kidney, and the risk of toxic reactions to this drug may be greater in patients with impaired renal function. Because elderly patients are more likely to have decreased renal function, care should be taken in dose selection, and it may be useful to monitor renal function [see Dosage and Administration (2.2)].

No dosage adjustment is recommended for elderly patients.

8.6 Renal Impairment

Varenicline is substantially eliminated by renal glomerular filtration along with active tubular secretion. Dose reduction is not required in patients with mild to moderate renal impairment. For patients with severe renal impairment (estimated creatinine clearance <30 mL/min), and for patients with end-stage renal disease undergoing hemodialysis, dosage adjustment is needed. [see Dosage and Administration (2.2) and Clinical Pharmacology (12.3)].

9 DRUG ABUSE AND DEPENDENCE

9.1 Controlled Substance

Varenicline is not a controlled substance.

9.3 Dependence

Humans: Fewer than 1 out of 1000 patients reported euphoria in clinical trials with CHANTIX. At higher doses (greater than 2 mg), CHANTIX produced more frequent reports of gastrointestinal disturbances such as nausea and vomiting. There is no evidence of dose-escalation to maintain therapeutic effects in clinical studies, which suggests that tolerance does not develop. Abrupt discontinuation of CHANTIX was associated with an increase in irritability and sleep disturbances in up to 3% of patients. This suggests that, in some patients, varenicline may produce mild physical dependence which is not associated with addiction.

In a human laboratory abuse liability study, a single oral dose of 1 mg varenicline did not produce any significant positive or negative subjective responses in smokers. In non-smokers, 1 mg varenicline produced an increase in some positive subjective effects, but this was accompanied by an increase in negative adverse effects, especially nausea. A single oral dose of 3 mg varenicline uniformly produced unpleasant subjective responses in both smokers and non-smokers.

Animals: Studies in rodents have shown that varenicline produces behavioral responses similar to those produced by nicotine. In rats trained to discriminate nicotine from saline, varenicline produced full generalization to the nicotine cue. In self-administration studies, the degree to which varenicline substitutes for nicotine is dependent upon the requirement of the task. Rats trained to self-administer nicotine under easy conditions continued to self-administer varenicline to a degree comparable to that of nicotine; however in a more demanding task, rats self-administered varenicline to a lesser extent than nicotine. Varenicline pretreatment also reduced nicotine self-administration.

10 OVERDOSAGE

In case of overdose, standard supportive measures should be instituted as required.

Varenicline has been shown to be dialyzed in patients with end stage renal disease [see Clinical Pharmacology (12.3)], however, there is no experience in dialysis following overdose.

11 DESCRIPTION

CHANTIX tablets contain varenicline (as the tartrate salt), which is a partial agonist selective for α4β2 nicotinic acetylcholine receptor subtypes.

Varenicline, as the tartrate salt, is a powder which is a white to off-white to slightly yellow solid with the following chemical name: 7,8,9,10-tetrahydro-6,10-methano-6H-pyrazino[2,3- h][3]benzazepine, (2R,3R)-2,3-dihydroxybutanedioate (1:1). It is highly soluble in water. Varenicline tartrate has a molecular weight of 361.35 Daltons, and a molecular formula of C13H13N3 ∙ C4H6O6. The chemical structure is:

CHANTIX is supplied for oral administration in two strengths: a 0.5 mg capsular biconvex, white to off-white, film-coated tablet debossed with "Pfizer" on one side and "CHX 0.5" on the other side and a 1 mg capsular biconvex, light blue film-coated tablet debossed with "Pfizer" on one side and "CHX 1.0" on the other side. Each 0.5 mg CHANTIX tablet contains 0.85 mg of varenicline tartrate equivalent to 0.5 mg of varenicline free base; each 1mg CHANTIX tablet contains 1.71 mg of varenicline tartrate equivalent to 1 mg of varenicline free base. The following inactive ingredients are included in the tablets: microcrystalline cellulose, anhydrous dibasic calcium phosphate, croscarmellose sodium, colloidal silicon dioxide, magnesium stearate, Opadry® White (for 0.5 mg), Opadry® Blue (for 1 mg), and Opadry® Clear.

12 CLINICAL PHARMACOLOGY

12.1 Mechanism of Action

Varenicline binds with high affinity and selectivity at α4β2 neuronal nicotinic acetylcholine receptors. The efficacy of CHANTIX in smoking cessation is believed to be the result of varenicline's activity at α4β2 sub-type of the nicotinic receptor where its binding produces agonist activity, while simultaneously preventing nicotine binding to these receptors.

Electrophysiology studies in vitro and neurochemical studies in vivo have shown that varenicline binds to α4β2 neuronal nicotinic acetylcholine receptors and stimulates receptor-mediated activity, but at a significantly lower level than nicotine. Varenicline blocks the ability of nicotine to activate α4β2 receptors and thus to stimulate the central nervous mesolimbic dopamine system, believed to be the neuronal mechanism underlying reinforcement and reward experienced upon smoking. Varenicline is highly selective and binds more potently to α4β2 receptors than to other common nicotinic receptors (>500-fold α3β4, >3500-fold α7, >20,000-fold α1βγδ), or to non-nicotinic receptors and transporters (>2000-fold). Varenicline also binds with moderate affinity (Ki = 350 nM) to the 5-HT3 receptor.

12.3 Pharmacokinetics

Absorption/Distribution: Maximum plasma concentrations of varenicline occur typically within 3–4 hours after oral administration. Following administration of multiple oral doses of varenicline, steady-state conditions were reached within 4 days. Over the recommended dosing range, varenicline exhibits linear pharmacokinetics after single or repeated doses. In a mass balance study, absorption of varenicline was virtually complete after oral administration and systemic availability was ~90%. Oral bioavailability of varenicline is unaffected by food or time-of-day dosing. Plasma protein binding of varenicline is low (≤20%) and independent of both age and renal function.

Metabolism/Elimination: The elimination half-life of varenicline is approximately 24 hours. Varenicline undergoes minimal metabolism, with 92% excreted unchanged in the urine. Renal elimination of varenicline is primarily through glomerular filtration along with active tubular secretion possibly via the organic cation transporter, OCT2.

Pharmacokinetics in Special Patient Populations: There are no clinically meaningful differences in varenicline pharmacokinetics due to age, race, gender, smoking status, or use of concomitant medications, as demonstrated in specific pharmacokinetic studies and in population pharmacokinetic analyses.

Renal Impairment: Varenicline pharmacokinetics were unchanged in subjects with mild renal impairment (estimated creatinine clearance >50 mL/min and ≤80 mL/min). In subjects with moderate renal impairment (estimated creatinine clearance ≥30 mL/min and ≤50 mL/min), varenicline exposure increased 1.5-fold compared with subjects with normal renal function (estimated creatinine clearance >80 mL/min). In subjects with severe renal impairment (estimated creatinine clearance <30 mL/min), varenicline exposure was increased 2.1-fold. In subjects with end-stage-renal disease (ESRD) undergoing a three-hour session of hemodialysis for three days a week, varenicline exposure was increased 2.7-fold following 0.5 mg once daily administration for 12 days. The plasma Cmax and AUC of varenicline noted in this setting were similar to those of healthy subjects receiving 1 mg twice daily. [see Dosage and Administration (2.2), and Use in Specific Populations (8.6)]. Additionally, in subjects with ESRD, varenicline was efficiently removed by hemodialysis [see Overdosage (10)].

Geriatric Patients: A combined single- and multiple-dose pharmacokinetic study demonstrated that the pharmacokinetics of 1 mg varenicline given once daily or twice daily to 16 healthy elderly male and female smokers (aged 65–75 yrs) for 7 consecutive days was similar to that of younger subjects.

Pediatric Patients: Because the safety and effectiveness of CHANTIX in pediatric patients have not been established, CHANTIX is not recommended for use in patients under 18 years of age. Single and multiple-dose pharmacokinetics of varenicline have been investigated in pediatric patients aged 12 to 17 years old (inclusive) and were approximately dose-proportional over the 0.5 mg to 2 mg daily dose range studied. Steady-state systemic exposure in adolescent patients of bodyweight >55 kg, as assessed by AUC (0–24), was comparable to that noted for the same doses in the adult population. When 0.5 mg BID was given, steady-state daily exposure of varenicline was, on average, higher (by approximately 40%) in adolescent patients with bodyweight ≤ 55 kg compared to that noted in the adult population.

Hepatic Impairment: Due to the absence of significant hepatic metabolism, varenicline pharmacokinetics should be unaffected in patients with hepatic impairment.

Drug-Drug Interactions: Drug interaction studies were performed with varenicline and digoxin, warfarin, transdermal nicotine, bupropion, cimetidine, and metformin. No clinically meaningful pharmacokinetic drug-drug interactions have been identified.

In vitro studies demonstrated that varenicline does not inhibit the following cytochrome P450 enzymes (IC50 >6400 ng/mL): 1A2, 2A6, 2B6, 2C8, 2C9, 2C19, 2D6, 2E1, and 3A4/5. Also, in human hepatocytes in vitro, varenicline does not induce the cytochrome P450 enzymes 1A2 and 3A4.

In vitro studies demonstrated that varenicline does not inhibit human renal transport proteins at therapeutic concentrations. Therefore, drugs that are cleared by renal secretion (e.g., metformin [see below]) are unlikely to be affected by varenicline.

In vitro studies demonstrated the active renal secretion of varenicline is mediated by the human organic cation transporter OCT2. Co-administration with inhibitors of OCT2 (e.g., cimeditine [see below]) may not necessitate a dose adjustment of CHANTIX as the increase in systemic exposure to CHANTIX is not expected to be clinically meaningful. Furthermore, since metabolism of varenicline represents less than 10% of its clearance, drugs known to affect the cytochrome P450 system are unlikely to alter the pharmacokinetics of CHANTIX [see Clinical Pharmacology (12.3)]; therefore, a dose adjustment of CHANTIX would not be required.

Metformin: When co-administered to 30 smokers, varenicline (1 mg twice daily) did not alter the steady-state pharmacokinetics of metformin (500 mg twice daily), which is a substrate of OCT2. Metformin had no effect on varenicline steady-state pharmacokinetics.

Cimetidine: Co-administration of an OCT2 inhibitor, cimetidine (300 mg four times daily), with varenicline (2 mg single dose) to 12 smokers increased the systemic exposure of varenicline by 29% (90% CI: 21.5%, 36.9%) due to a reduction in varenicline renal clearance.

Digoxin: Varenicline (1 mg twice daily) did not alter the steady-state pharmacokinetics of digoxin administered as a 0.25 mg daily dose in 18 smokers.

Warfarin: Varenicline (1 mg twice daily) did not alter the pharmacokinetics of a single 25 mg dose of (R, S)-warfarin in 24 smokers. Prothrombin time (INR) was not affected by varenicline. Smoking cessation itself may result in changes to warfarin pharmacokinetics [see Drug Interactions (7.2)].

Use with Other Drugs for Smoking Cessation:

Bupropion: Varenicline (1 mg twice daily) did not alter the steady-state pharmacokinetics of bupropion (150 mg twice daily) in 46 smokers [see Drug Interactions (7.1)].

Nicotine replacement therapy (NRT): Although co-administration of varenicline (1 mg twice daily) and transdermal nicotine (21 mg/day) for up to 12 days did not affect nicotine pharmacokinetics, the incidence of adverse reactions was greater for the combination than for NRT alone [see Drug Interactions (7.1)].

13 NONCLINICAL TOXICOLOGY

13.1 Carcinogenesis, Mutagenesis, Impairment of Fertility

Carcinogenesis: Lifetime carcinogenicity studies were performed in CD-1 mice and Sprague-Dawley rats. There was no evidence of a carcinogenic effect in mice administered varenicline by oral gavage for 2 years at doses up to 20 mg/kg/day (47 times the maximum recommended human daily exposure based on AUC). Rats were administered varenicline (1, 5, and 15 mg/kg/day) by oral gavage for 2 years. In male rats (n = 65 per sex per dose group), incidences of hibernoma (tumor of the brown fat) were increased at the mid dose (1 tumor, 5 mg/kg/day, 23 times the maximum recommended human daily exposure based on AUC) and maximum dose (2 tumors, 15 mg/kg/day, 67 times the maximum recommended human daily exposure based on AUC). The clinical relevance of this finding to humans has not been established. There was no evidence of carcinogenicity in female rats.

Mutagenesis: Varenicline was not genotoxic, with or without metabolic activation, in the following assays: Ames bacterial mutation assay; mammalian CHO/HGPRT assay; and tests for cytogenetic aberrations in vivo in rat bone marrow and in vitro in human lymphocytes.

Impairment of Fertility: There was no evidence of impairment of fertility in either male or female Sprague-Dawley rats administered varenicline succinate up to 15 mg/kg/day (67 and 36 times, respectively, the maximum recommended human daily exposure based on AUC at 1 mg twice daily). However, a decrease in fertility was noted in the offspring of pregnant rats who were administered varenicline succinate at an oral dose of 15 mg/kg/day (36 times the maximum recommended human daily exposure based on AUC at 1 mg twice daily). This decrease in fertility in the offspring of treated female rats was not evident at an oral dose of 3 mg/kg/day (9 times the maximum recommended human daily exposure based on AUC at 1 mg twice daily).

14 CLINICAL STUDIES

The efficacy of CHANTIX in smoking cessation was demonstrated in six clinical trials in which a total of 3659 chronic cigarette smokers (≥10 cigarettes per day) were treated with CHANTIX. In all clinical studies, abstinence from smoking was determined by patient self-report and verified by measurement of exhaled carbon monoxide (CO≤10 ppm) at weekly visits. Among the CHANTIX-treated patients enrolled in these studies, the completion rate was 65%. Except for the dose-ranging study (Study 1) and the maintenance of abstinence study (Study 6), patients were treated for 12 weeks and then were followed for 40 weeks post-treatment. Most patients enrolled in these trials were white (79–96%). All studies enrolled almost equal numbers of men and women. The average age of patients in these studies was 43 years. Patients on average had smoked about 21 cigarettes per day for an average of approximately 25 years. Patients set a date to stop smoking (target quit date) with dosing starting 1 week before this date.

Three additional studies were conducted in patients with cardiovascular disease, in patients with chronic obstructive pulmonary disease [see Clinical Studies (14.4)], and in patients instructed to select their quit date within days 8 and 35 of treatment [see Clinical Studies (14.5)].

In all studies, patients were provided with an educational booklet on smoking cessation and received up to 10 minutes of smoking cessation counseling at each weekly treatment visit according to Agency for Healthcare Research and Quality guidelines.

14.1 Initiation of Abstinence

Study 1: This was a six-week dose-ranging study comparing CHANTIX to placebo. This study provided initial evidence that CHANTIX at a total dose of 1 mg per day or 2 mg per day was effective as an aid to smoking cessation.

Study 2: This study of 627 patients compared CHANTIX 1 mg per day and 2 mg per day with placebo. Patients were treated for 12 weeks (including one week titration) and then were followed for 40 weeks post-treatment. CHANTIX was given in two divided doses daily. Each dose of CHANTIX was given in two different regimens, with and without initial dose titration, to explore the effect of different dosing regimens on tolerability. For the titrated groups, dosage was titrated up over the course of one week, with full dosage achieved starting with the second week of dosing. The titrated and nontitrated groups were pooled for efficacy analysis.

Forty-five percent of patients receiving CHANTIX 1 mg per day (0.5 mg twice daily) and 51% of patients receiving 2 mg per day (1 mg twice daily) had CO-confirmed continuous abstinence during weeks 9 through 12 compared to 12% of patients in the placebo group (Figure 1). In addition, 31% of the 1 mg per day group and 31% of the 2 mg per day group were continuously abstinent from one week after TQD through the end of treatment as compared to 8% of the placebo group.

Study 3: This flexible-dosing study of 312 patients examined the effect of a patient-directed dosing strategy of CHANTIX or placebo. After an initial one-week titration to a dose of 0.5 mg twice daily, patients could adjust their dosage as often as they wished between 0.5 mg once daily to 1 mg twice daily per day. Sixty-nine percent of patients titrated to the maximum allowable dose at any time during the study. For 44% of patients, the modal dose selected was 1 mg twice daily; for slightly over half of the study participants, the modal dose selected was 1 mg/day or less.

Of the patients treated with CHANTIX, 40% had CO-confirmed continuous abstinence during weeks 9 through 12 compared to 12% in the placebo group. In addition, 29% of the CHANTIX group were continuously abstinent from one week after TQD through the end of treatment as compared to 9% of the placebo group.

Study 4 and Study 5: These identical double-blind studies compared CHANTIX 2 mg per day, bupropion sustained-release (SR) 150 mg twice daily, and placebo. Patients were treated for 12 weeks and then were followed for 40 weeks post-treatment. The CHANTIX dosage of 1 mg twice daily was achieved using a titration of 0.5 mg once daily for the initial 3 days followed by 0.5 mg twice daily for the next 4 days. The bupropion SR dosage of 150 mg twice daily was achieved using a 3-day titration of 150 mg once daily. Study 4 enrolled 1022 patients and Study 5 enrolled 1023 patients. Patients inappropriate for bupropion treatment or patients who had previously used bupropion were excluded.

In Study 4, patients treated with CHANTIX had a superior rate of CO-confirmed abstinence during weeks 9 through 12 (44%) compared to patients treated with bupropion SR (30%) or placebo (17%). The bupropion SR quit rate was also superior to placebo. In addition, 29% of the CHANTIX group were continuously abstinent from one week after TQD through the end of treatment as compared to 12% of the placebo group and 23% of the bupropion SR group.

Similarly in Study 5, patients treated with CHANTIX had a superior rate of CO-confirmed abstinence during weeks 9 through 12 (44%) compared to patients treated with bupropion SR (30%) or placebo (18%). The bupropion SR quit rate was also superior to placebo. In addition, 29% of the CHANTIX group were continuously abstinent from one week after TQD through the end of treatment as compared to 11% of the placebo group and 21% of the bupropion SR group.

Figure 1: Continuous Abstinence, Weeks 9 through 12

Table 6: Continuous Abstinence, Weeks 9 through 12 (95% confidence interval)

Table 6: Continuous Abstinence, Weeks 9 through 12 (95% confidence interval)
 | CHANTIX 0.5 mg BID | CHANTIX 1 mg BID | CHANTIX Flexible | Bupropion SR | Placebo
Study 2 | 45% (39%, 51%) | 51% (44%, 57%) |  |  | 12% (6%, 18%)
Study 3 |  |  | 40% (32%, 48%) |  | 12% (7%, 17%)
Study 4 |  | 44% (38%, 49%) |  | 30% (25%, 35%) | 17% (13%, 22%)
Study 5 |  | 44% (38%, 49%) |  | 30% (25%, 35%) | 18% (14%, 22%)
BID = twice daily

14.2 Urge to Smoke

Based on responses to the Brief Questionnaire of Smoking Urges and the Minnesota Nicotine Withdrawal scale "urge to smoke" item, CHANTIX reduced urge to smoke compared to placebo.

14.3 Long-Term Abstinence

Studies 1 through 5 included 40 weeks of post-treatment follow-up. In each study, CHANTIX-treated patients were more likely to maintain abstinence throughout the follow-up period than were patients treated with placebo (Figure 2, Table 7).

Figure 2: Continuous Abstinence, Weeks 9 through 52

Table 7: Continuous Abstinence, Weeks 9 through 52 (95% confidence interval) across different studies

Table 7: Continuous Abstinence, Weeks 9 through 52 (95% confidence interval) across different studies
 | CHANTIX 0.5 mg BID | CHANTIX 1 mg BID | CHANTIX Flexible | Bupropion SR | Placebo
Study 2 | 19% (14%, 24%) | 23% (18%, 28%) |  |  | 4% (1%, 8%)
Study 3 |  |  | 22% (16%, 29%) |  | 8% (3%, 12%)
Study 4 |  | 21% (17%, 26%) |  | 16% (12%, 20%) | 8% (5%, 11%)
Study 5 |  | 22% (17%, 26%) |  | 14% (11%, 18%) | 10% (7%, 13%)
BID = twice daily

Study 6: This study assessed the effect of an additional 12 weeks of CHANTIX therapy on the likelihood of long-term abstinence. Patients in this study (n=1927) were treated with open-label CHANTIX 1 mg twice daily for 12 weeks. Patients who had stopped smoking for at least a week by Week 12 (n= 1210) were then randomized to double-blind treatment with CHANTIX (1 mg twice daily) or placebo for an additional 12 weeks and then followed for 28 weeks post-treatment.

The continuous abstinence rate from Week 13 through Week 24 was higher for patients continuing treatment with CHANTIX (70%) than for patients switching to placebo (50%). Superiority to placebo was also maintained during 28 weeks post-treatment follow-up (CHANTIX 54% versus placebo 39%).

In Figure 3 below, the x-axis represents the study week for each observation, allowing a comparison of groups at similar times after discontinuation of CHANTIX; post-CHANTIX follow-up begins at Week 13 for the placebo group and Week 25 for the CHANTIX group. The y-axis represents the percentage of patients who had been abstinent for the last week of CHANTIX treatment and remained abstinent at the given timepoint.

Figure 3: Continuous Abstinence Rate during Nontreatment Follow-Up

14.4 Subjects with Cardiovascular and Chronic Obstructive Pulmonary Disease

CHANTIX was evaluated in a randomized, double-blind, placebo-controlled study of subjects aged 35 to 75 years with stable, documented cardiovascular disease (diagnoses other than, or in addition to, hypertension) that had been diagnosed for more than 2 months. Subjects were randomized to CHANTIX 1 mg twice daily (n=353) or placebo (n=350) for a treatment of 12 weeks and then were followed for 40 weeks post-treatment. Subjects treated with CHANTIX had a superior rate of CO-confirmed abstinence during weeks 9 through 12 (47%) compared to subjects treated with placebo (14%) and from week 9 through 52 (20%) compared to subjects treated with placebo (7%).

CHANTIX was evaluated in a randomized, double-blind, placebo-controlled study of subjects aged ≥ 35 years with mild-to-moderate COPD with post-bronchodilator FEV1/FVC <70% and FEV1 ≥ 50% of predicted normal value. Subjects were randomized to CHANTIX 1 mg twice daily (n=223) or placebo (n=237) for a treatment of 12 weeks and then were followed for 40 weeks post-treatment. Subjects treated with CHANTIX had a superior rate of CO-confirmed abstinence during weeks 9 through 12 (41%) compared to subjects treated with placebo (9%) and from week 9 through 52 (19%) compared to subjects treated with placebo (6%).

Table 8: Continuous Abstinence (95% confidence interval), Studies in Patients with Cardiovascular Disease (CVD) and Chronic Obstructive Pulmonary Disease (COPD)
 | Weeks 9 through 12 |  | Weeks 9 through 52
 | CHANTIX 1 mg BID | Placebo | CHANTIX 1 mg BID | Placebo
CVD Study | 47% (42%, 53%) | 14% (11%, 18%) | 20% (16%, 24%) | 7% (5%, 10%)
COPD Study | 41% (34%, 47%) | 9% (6%, 13%) | 19% (14%, 24%) | 6% (3%, 9%)
BID = twice daily

14.5 Subjects with Major Depressive Disorder

CHANTIX was evaluated in a randomized, double-blind, placebo-controlled study of subjects aged 18 to 75 years with major depressive disorder without psychotic features (DSM-IV TR). If on medication, subjects were to be on a stable antidepressant regimen for at least two months. If not on medication, subjects were to have experienced a major depressive episode in the past 2 years, which was successfully treated. Subjects were randomized to CHANTIX 1 mg twice daily (n=256) or placebo (n=269) for a treatment of 12 weeks and then followed for 40 weeks post-treatment. Subjects treated with CHANTIX had a superior rate of CO-confirmed abstinence during weeks 9 through 12 (36%) compared to subjects treated with placebo (16%) and from week 9 through 52 (20%) compared to subjects treated with placebo (10%).

Table 9: Continuous Abstinence (95% confidence interval), Study in Patients with Major Depressive Disorder (MDD)
 | Weeks 9 through 12 |  | Weeks 9 through 52
 | CHANTIX 1 mg BID | Placebo | CHANTIX 1 mg BID | Placebo
MDD Study | 36% (30%, 42%) | 16% (11%, 20%) | 20% (15%, 25%) | 10% (7%, 14%)
BID = twice daily

14.6 Alternative Instructions for Setting a Quit Date

CHANTIX was evaluated in a double-blind, placebo-controlled trial where patients were instructed to select a target quit date between Day 8 and Day 35 of treatment. Subjects were randomized 3:1 to CHANTIX 1 mg twice daily (n=486) or placebo (n=165) for 12 weeks of treatment and followed for another 12 weeks post-treatment. Patients treated with CHANTIX had a superior rate of CO-confirmed abstinence during weeks 9 through 12 (54%) compared to patients treated with placebo (19%) and from weeks 9 through 24 (35%) compared to subjects treated with placebo (13%).

14.7 Re-Treatment Study

CHANTIX was evaluated in a double-blind, placebo-controlled trial of patients who had made a previous attempt to quit smoking with CHANTIX, and either did not succeed in quitting or relapsed after treatment. Subjects were randomized 1:1 to CHANTIX 1 mg twice daily (n=249) or placebo (n=245) for 12 weeks of treatment and followed for 40 weeks post-treatment. Patients included in this study had taken CHANTIX for a smoking-cessation attempt in the past (for a total treatment duration of a minimum of two weeks), at least three months prior to study entry, and had been smoking for at least four weeks.

Patients treated with CHANTIX had a superior rate of CO-confirmed abstinence during weeks 9 through 12 (45%) compared to patients treated with placebo (12%) and from weeks 9 through 52 (20%) compared to subjects treated with placebo (3%).

Table 10: Continuous Abstinence (95% confidence interval), Re-Treatment Study
 | Weeks 9 through 12 |  | Weeks 9 through 52
 | CHANTIX 1 mg BID | Placebo | CHANTIX 1 mg BID | Placebo
Retreatment Study | 45% (39%, 51%) | 12% (8%, 16%) | 20% (15%, 25%) | 3% (1%, 5%)
BID = twice daily

16 HOW SUPPLIED/STORAGE AND HANDLING

CHANTIX is supplied for oral administration in two strengths: a 0.5 mg capsular biconvex, white to off-white, film-coated tablet debossed with "Pfizer" on one side and "CHX 0.5" on the other side and a 1 mg capsular biconvex, light blue film-coated tablet debossed with "Pfizer" on one side and "CHX 1.0" on the other side. CHANTIX is supplied in the following package configurations:

 | Description | NDC
 | Starting 4-week card: 0.5 mg × 11 tablets and 1 mg × 42 tablets | NDC 63187-618-53
 | Starting Month Box: 0.5 mg × 11 tablets and 1 mg × 42 tablets | NDC 63187-618-53

STORAGE AND HANDLING

Store at 25°C (77°F); excursions permitted to 15–30°C (59–86°F) (see USP Controlled Room Temperature).

17 PATIENT COUNSELING INFORMATION

See FDA-approved patient labeling (Medication Guide)

Initiate Treatment and Continue to Attempt to Quit if Lapse

Instruct patients to set a date to quit smoking and to initiate CHANTIX treatment one week before the quit date. Alternatively, the patient can begin CHANTIX dosing and then set a date to quit smoking between days 8 and 35 of treatment. Encourage patients to continue to attempt to quit if they have early lapses after quit day [see Dosage and Administration (2.1)]. Encourage patients who are motivated to quit and who did not succeed in stopping smoking during prior CHANTIX therapy for reasons other than intolerability due to adverse events, or who relapsed after treatment to make another attempt with CHANTIX once factors contributing to the failed attempt have been identified and addressed [see Dosage and Administration (2.1), Clinical Studies (14.7)].

How To Take

Advise patients that CHANTIX should be taken after eating, and with a full glass of water [see Dosage and Administration (2.1)].

Starting Week Dosage

Instruct patients on how to titrate CHANTIX, beginning at a dose of 0.5 mg/day. Explain that one 0.5 mg tablet should be taken daily for the first three days, and that for the next four days, one 0.5 mg tablet should be taken in the morning and one 0.5 mg tablet should be taken in the evening [see Dosage and Administration (2.1)].

Continuing Weeks Dosage

Advise patients that, after the first seven days, the dose should be increased to one 1 mg tablet in the morning and one 1 mg tablet in the evening [see Dosage and Administration (2.1)].

Dosage Adjustment for CHANTIX or Other Drugs

Inform patients that nausea and insomnia are side effects of CHANTIX and are usually transient; however, advise patients that if they are persistently troubled by these symptoms, they should notify the prescribing physician so that a dose reduction can be considered.

Inform patients that some drugs may require dose adjustment after quitting smoking [see Dosage and Administration (2.1)].

Counseling and Support

Provide patients with educational materials and necessary counseling to support an attempt at quitting smoking [see Dosage and Administration (2.1)].

Neuropsychiatric Symptoms

Inform patients that some patients have experienced changes in mood (including depression and mania), psychosis, hallucinations, paranoia, delusions, homicidal ideation, aggression, anxiety, and panic, as well as suicidal ideation and suicide when attempting to quit smoking while taking CHANTIX. If patients develop agitation, hostility, depressed mood, or changes in behavior or thinking that are not typical for them, or if patients develop suicidal ideation or behavior, they should be urged to discontinue CHANTIX and report these symptoms to their healthcare provider immediately [see Boxed Warning, Warnings and Precautions (5.1), Adverse Reactions (6.2)].

History of Psychiatric Illness

Encourage patients to reveal any history of psychiatric illness prior to initiating treatment.

Nicotine Withdrawal

Inform patients that quitting smoking, with or without CHANTIX, may be associated with nicotine withdrawal symptoms (including depression or agitation) or exacerbation of pre-existing psychiatric illness.

Seizures

Encourage patients to report any history of seizures or other factors that can lower seizure threshold. Instruct patients to discontinue CHANTIX and contact a healthcare provider immediately if they experience a seizure while on treatment [see Warnings and Precautions (5.2)].

Interaction with Alcohol

Advise patients to reduce the amount of alcohol they consume while taking CHANTIX until they know whether CHANTIX affects their tolerance for alcohol [see Warnings and Precautions (5.3), Adverse Reactions (6.2)].

Driving or Operating Machinery

Advise patients to use caution driving or operating machinery until they know how quitting smoking and/or varenicline may affect them [see Warnings and Precautions (5.4)].

Cardiovascular Events

Patients should be instructed to notify their health care providers of symptoms of new or worsening cardiovascular events and to seek immediate medical attention if they experience signs and symptoms of myocardial infarction or stroke. [see Warnings and Precautions (5.5), and Adverse Reactions (6.1)].

Angioedema

Inform patients that there have been reports of angioedema, with swelling of the face, mouth (lip, gum, tongue) and neck (larynx and pharynx) that can lead to life-threatening respiratory compromise. Instruct patients to discontinue CHANTIX and immediately seek medical care if they experience these symptoms [see Warnings and Precautions (5.2), and Adverse Reactions (6.2)].

Serious Skin Reactions

Inform patients that serious skin reactions, such as Stevens-Johnson Syndrome and erythema multiforme, were reported by some patients taking CHANTIX. Advise patients to stop taking CHANTIX at the first sign of rash with mucosal lesions or skin reaction and contact a healthcare provider immediately [see Warnings and Precautions (5.3), and Adverse Reactions (6.2)].

Vivid, Unusual, or Strange Dreams

Inform patients that they may experience vivid, unusual or strange dreams during treatment with CHANTIX.

Pregnancy and Lactation

Patients who are pregnant or breastfeeding or planning to become pregnant should be advised of: the risks of smoking to a pregnant mother and her developing baby, the potential risks of CHANTIX use during pregnancy and breastfeeding, and the benefits of smoking cessation with and without CHANTIX [see Use in Specific Populations (8.1 and 8.3)].

This product's label may have been updated. For full prescribing information, please visit www.pfizer.com

LAB- 0327-20.0

MEDICATION GUIDE

CHANTIX® (CHANT-iks)
(varenicline) Tablets

What is the most important information I should know about CHANTIX?

Some people have had serious side effects while using CHANTIX to help them quit smoking, including:

New or worse mental health problems, such as changes in behavior, hostility, agitation, depressed mood, and suicidal thoughts or actions. Some people had these symptoms when they began taking CHANTIX, and others developed them after several weeks of treatment, or after stopping CHANTIX.

Before taking CHANTIX, tell your doctor if you have ever had depression or other mental health problems. You should also tell your doctor about any symptoms you had during other times you tried to quit smoking, with or without CHANTIX.

Stop taking CHANTIX and call your doctor right away if you, your family, or caregiver notice agitation, hostility, depression or changes in your behavior or thinking that are not typical for you, or you develop any of the following symptoms:

- thoughts about suicide or dying, or attempts to commit suicide
- new or worse depression, anxiety, or panic attacks
- feeling very agitated or restless
- acting aggressive, being angry, or violent
- acting on dangerous impulses
- an extreme increase in activity and talking (mania)
- abnormal thoughts or sensations
- seeing or hearing things that are not there (hallucinations)
- feeling people are against you (paranoia)
- feeling confused
- other unusual changes in behavior or mood

When you try to quit smoking, with or without CHANTIX, you may have symptoms that may be due to nicotine withdrawal, including urge to smoke, depressed mood, trouble sleeping, irritability, frustration, anger, feeling anxious, difficulty concentrating, restlessness, decreased heart rate, and increased appetite or weight gain. Some people have even experienced suicidal thoughts when trying to quit smoking without medication. Sometimes quitting smoking can lead to worsening of mental health problems that you already have, such as depression.

See " What are the possible side effects of CHANTIX? " for more information about other side effects.

What is CHANTIX?

CHANTIX is a prescription medicine to help people stop smoking.

Quitting smoking can lower your chances of having lung disease, heart disease or getting certain types of cancer that are related to smoking.

It is not known if CHANTIX is safe and effective in children.

It is not known if CHANTIX is safe and effective when used with other stop smoking medicines.

Who should not take CHANTIX?

Do not take CHANTIX if you have had a serious allergic or skin reaction to CHANTIX. Symptoms may include:

- swelling of the face, mouth (tongue, lips, gums), throat or neck
- trouble breathing
- rash, with peeling skin
- blisters in your mouth

What should I tell my doctor before taking CHANTIX?

See "What is the most important information I should know about CHANTIX?"

Before you take CHANTIX, tell your doctor if you:

- use other treatments to quit smoking. Using CHANTIX with a nicotine patch may cause nausea, vomiting, headache, dizziness, upset stomach, and tiredness to happen more often than if you just use a nicotine patch alone.
- have kidney problems or get kidney dialysis. Your doctor may prescribe a lower dose of CHANTIX for you.
- have a history of seizures
- drink alcohol
- have heart or blood vessel problems
- have any other medical conditions
- are pregnant or plan to become pregnant. It is not known if CHANTIX will harm your unborn baby.
- are breastfeeding. It is not known if CHANTIX passes into breast milk. You and your doctor should decide if you will breastfeed or take CHANTIX. You should not do both.

Tell your doctor about all the medicines you take, including prescription and over the counter medicines, vitamins and herbal supplements. Your doctor may need to change the dose of some of your medicines when you stop smoking.

You should not use CHANTIX while using other medicines to quit smoking. Tell your doctor if you use other treatments to quit smoking.

Know the medicines you take. Keep a list of them with you to show your doctor and pharmacist when you get a new medicine.

How should I take CHANTIX?

- There are 2 ways that you can use CHANTIX to help you quit smoking. Talk to your doctor about the following 2 ways to use CHANTIX:
Choose a quit date when you will stop smoking. Start taking CHANTIX 1 week (7 days) before your quit date.
OR
Start taking CHANTIX before you choose a quit date. Pick a date to quit smoking that is between days 8 and 35 of treatment.
Starting CHANTIX before your quit date gives CHANTIX time to build up in your body. You can keep smoking during this time. Take CHANTIX exactly as prescribed by your doctor.
- CHANTIX comes as a white tablet (0.5 mg) and a blue tablet (1 mg). You start with the white tablet and then usually go to the blue tablet. See the chart below for dosing instructions for adults.

Day 1 to Day 3 | - White tablet (0.5 mg) - Take 1 tablet each day
Day 4 to Day 7 | - White tablet (0.5 mg) - Take 1 in the morning and 1 in the evening
Day 8 to end of treatment | - Blue tablet (1 mg) - Take 1 in the morning and 1 in the evening

- Make sure that you try to stop smoking on your quit date. If you slip-up and smoke, try again. Some people need to take CHANTIX for a few weeks for CHANTIX to work best.
- Most people will take CHANTIX for up to 12 weeks. If you have completely quit smoking by 12 weeks, your doctor may prescribe CHANTIX for another 12 weeks to help you stay cigarette-free.
- Take CHANTIX after eating and with a full glass (8 ounces) of water.
- This dosing schedule may not be right for everyone. Talk to your doctor if you are having side effects such as nausea, strange dreams, or sleep problems. Your doctor may want to reduce your dose.
- If you miss a dose of CHANTIX, take it as soon as you remember. If it is almost time for your next dose, skip the missed dose. Just take your next dose at your regular time.

What should I avoid while taking CHANTIX?

- Use caution when driving or operating machinery until you know how CHANTIX affects you. CHANTIX may make you feel sleepy, dizzy, or have trouble concentrating, making it hard to drive or perform other activities safely.
- Decrease the amount of alcoholic beverages that you drink during treatment with CHANTIX until you know if CHANTIX affects your ability to tolerate alcohol. Some people have experienced the following when drinking alcohol during treatment with CHANTIX:
  - increased drunkenness (intoxication)
  - unusual or sometimes aggressive behavior
  - no memory of things that have happened

What are the possible side effects of CHANTIX?

Serious side effects of CHANTIX may include:

- See "What is the most important information I should know about CHANTIX?"
- Seizures. Some people have had seizures during treatment with CHANTIX. In most cases, the seizures have happened during the first month of treatment with CHANTIX. If you have a seizure during treatment with CHANTIX, stop taking CHANTIX and contact your healthcare provider right away.
- New or worse heart or blood vessel (cardiovascular) problems, mostly in people, who already have cardiovascular problems. Tell your doctor if you have any changes in symptoms during treatment with CHANTIX.
  Get emergency medical help right away if you have any of the following symptoms of a heart attack, including:
  - chest discomfort (uncomfortable pressure, squeezing, fullness or pain) that lasts more than a few minutes, or that goes away and comes back
  - pain or discomfort in one or both arms, back, neck, jaw or stomach
  - shortness of breath, sweating, nausea, vomiting, or feeling lightheaded associated with chest discomfort
- Allergic reactions can happen with CHANTIX. Some of these allergic reactions can be life-threatening.
- Serious skin reactions, including rash, swelling, redness, and peeling of the skin. Some of these skin reactions can become life-threatening.

Stop taking CHANTIX and get medical help right away if you have any of the following symptoms:

- swelling of the face, mouth (tongue, lips, and gums), throat or neck
- trouble breathing
- rash with peeling skin
- blisters in your mouth

The most common side effects of CHANTIX include:

- nausea
- sleep problems (trouble sleeping or vivid, unusual, or strange dreams)
- constipation
- gas
- vomiting

Tell your doctor about side effects that bother you or that do not go away.

These are not all the side effects of CHANTIX. Ask your doctor or pharmacist for more information.

Call your doctor for medical advice about side effects. You may report side effects to FDA at 1-800-FDA-1088.

How should I store CHANTIX?

- Store CHANTIX at room temperature, between 68°F to 77°F (20°C to 25°C).
- Keep CHANTIX and all medicines out of the reach of children.

General information about CHANTIX

Medicines are sometimes prescribed for purposes other than those listed in a Medication Guide. Do not use CHANTIX for a condition for which it was not prescribed. Do not give your CHANTIX to other people, even if they have the same symptoms that you have. It may harm them.

If you would like more information, talk with your doctor. You can ask your doctor or pharmacist for information about CHANTIX that is written for healthcare professionals.

For more information about CHANTIX and tips on how to quit smoking, go to www.CHANTIX.com or call 1-877-242-6849.

If you are motivated to quit smoking and did not succeed during prior CHANTIX treatment for reasons other than side effects, or if you returned to smoking after treatment, speak with your doctor about whether another course of CHANTIX therapy may be right for you.

What are the ingredients in CHANTIX?

Active ingredient: varenicline tartrate

Inactive ingredients: microcrystalline cellulose, anhydrous dibasic calcium phosphate, croscarmellose sodium, colloidal silicon dioxide, magnesium stearate, Opadry ® White (for 0.5 mg), Opadry ® Blue (for 1 mg), and Opadry® Clear.

This Medication Guide has been approved by the U.S. Food and Drug Administration.

October 2014

LAB-0328-13.0

Relabeled by:

Proficient Rx LP

Thousand Oaks, CA 91320

PRINCIPAL DISPLAY PANEL - 0.5 / 1 mg Starting Pack Carton

Contains:
1 Starting Week (0.5 mg* x 11 tablets)
3 Continuing Weeks (1 mg† x 42 tablets)

NDC 63187-618-53
Rx only

CHANTIX®
(varenicline) TABLETS

STARTING MONTH BOX
(Your first 4 weeks)

Use the Starting Week (green) blister card
first when beginning to take Chantix.

ALWAYS DISPENSE WITH ENCLOSED MEDICATION GUIDE